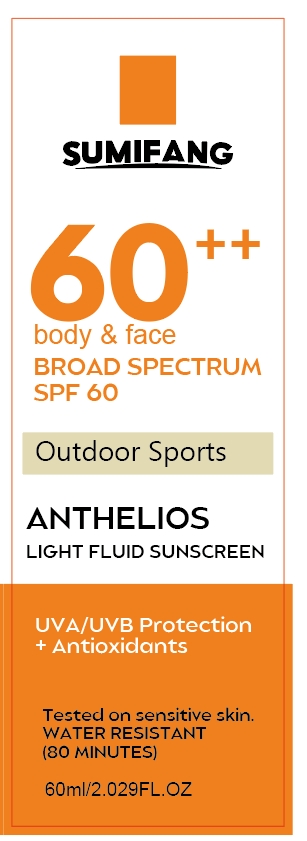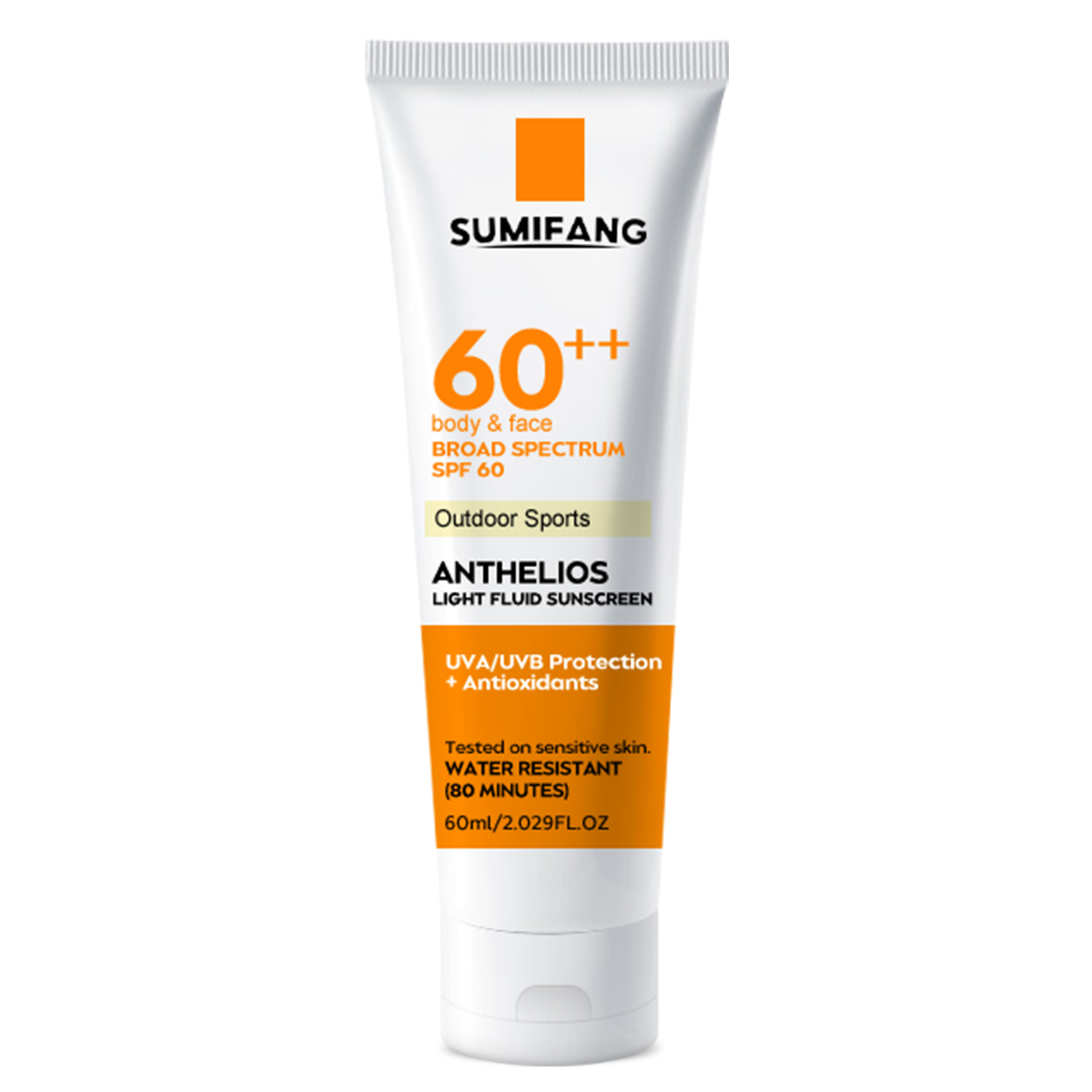 DRUG LABEL: SUNSCREEN
NDC: 84025-034 | Form: CREAM
Manufacturer: Guangzhou Yanxi Biotechnology Co., Ltd
Category: otc | Type: HUMAN OTC DRUG LABEL
Date: 20240429

ACTIVE INGREDIENTS: ZINC OXIDE 2 mg/50 mL; SQUALANE 5 mg/50 mL
INACTIVE INGREDIENTS: WATER

DOSAGE AND ADMINISTRATION

Apply to the face or body.

INACTIVE INGREDIENT

aqua

Keep out of reach of children.

WARNINGS

For external use only.

PURPOSE

helps prevent sunburn

INDICATIONS AND USAGE

Apply liberally 15 minutes before sun exposure. Reapply: After 80 minutes of swimming or sweating, Immediately after towel drying, At least every 2 hours.